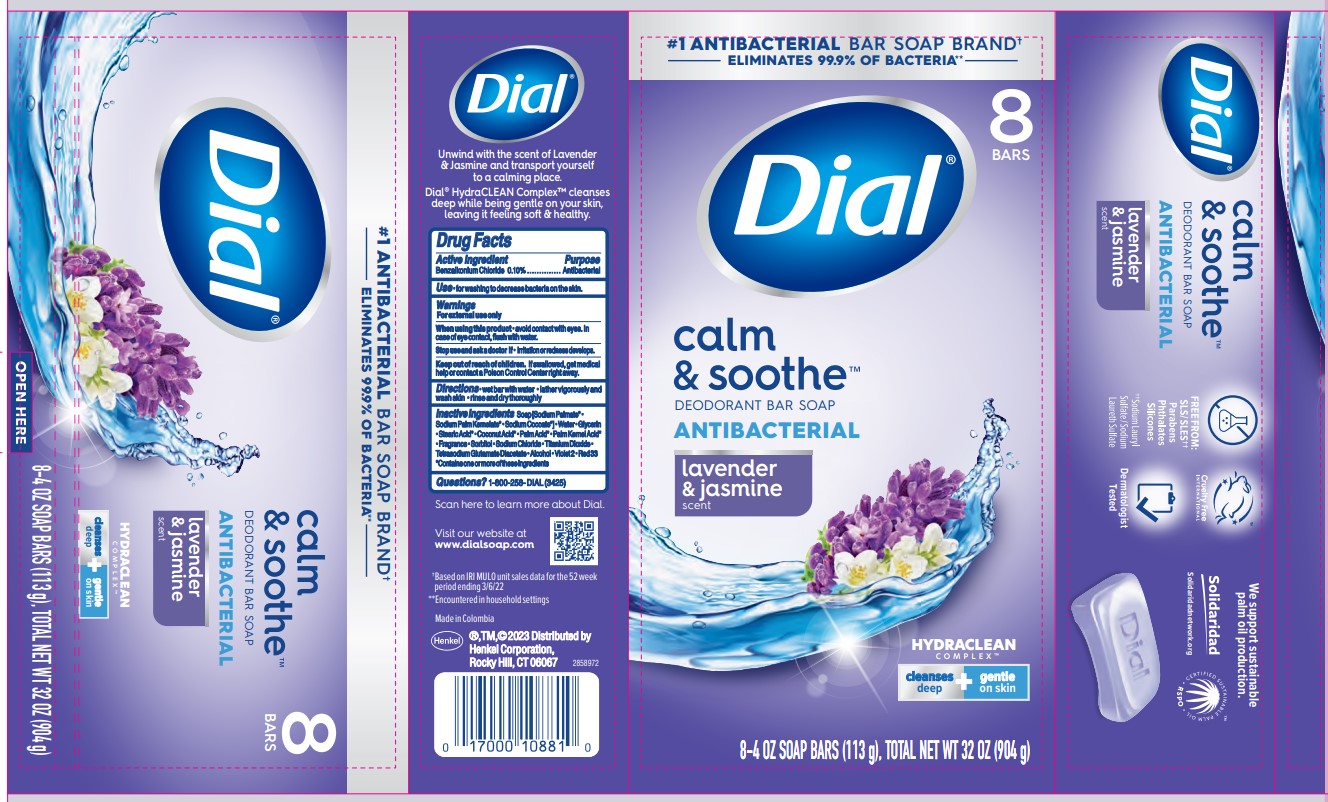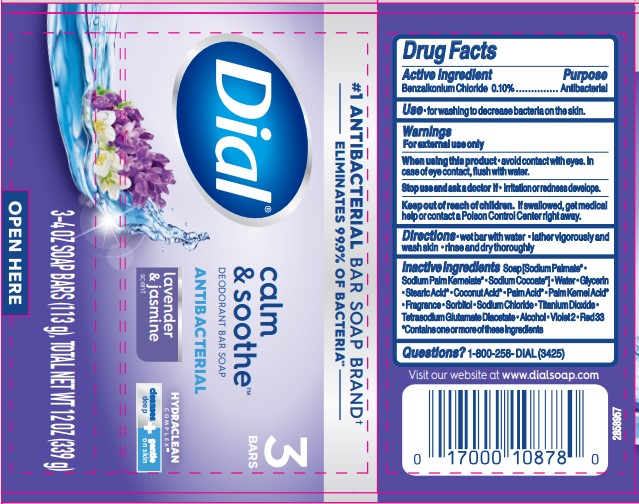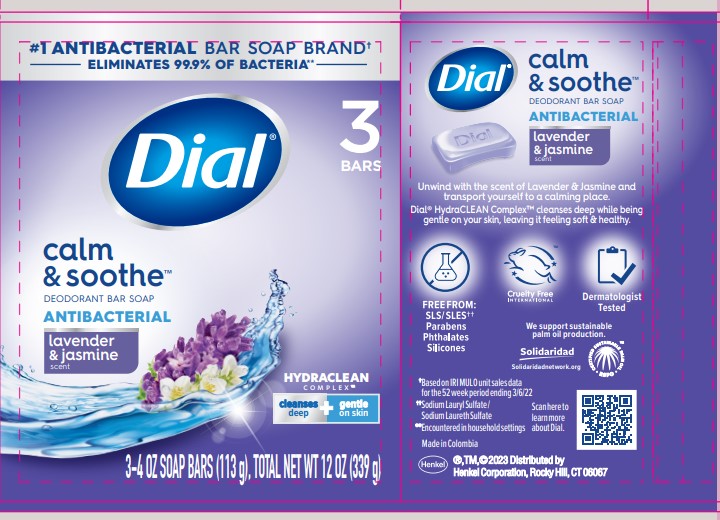 DRUG LABEL: Dial Antibacterial Calm and Soothe
NDC: 54340-266 | Form: SOAP
Manufacturer: Henkel Corporation
Category: otc | Type: HUMAN OTC DRUG LABEL
Date: 20251114

ACTIVE INGREDIENTS: BENZALKONIUM CHLORIDE 0.1 g/100 g
INACTIVE INGREDIENTS: ALCOHOL 0.01 g/100 g; SODIUM CHLORIDE 0.3898 g/100 g; SODIUM PALM KERNELATE 11.01 g/100 g; TITANIUM DIOXIDE 0.3 g/100 g; SORBITOL 0.55 g/100 g; GLYCERIN 8.1 g/100 g; SODIUM PALMATE 61.84 g/100 g; STEARIC ACID 2.435 g/100 g; WATER 13.95 g/100 g; TETRASODIUM GLUTAMATE DIACETATE 0.058 g/100 g; EXT. D&C VIOLET NO. 2 0.0068 g/100 g; D&C RED NO. 33 0.00092 g/100 g

Dial Calm & Soothe Antibacterial Soap, Dial Bar Lavender & Twilight Jasmine
Dial Antibacterial Deodorant Bar Soap Lavender & Twilight Jasmine
Dial Calm & Soothe Deodorant Bar Soap Antibacterial Lavender & Jasmine Scent

Drug Facts

Active ingredient

Benzalkonium Chloride 0.1%

Purpose

Antibacterial

Use

- for washing to decrease bacteria on the skin.

Warnings

For external use only

When using this product

- avoid contact with the eyes. In case of eye contact, flush with water.

Stop use and ask a doctor if

- irritation and redness develops.

Keep out of reach of children. If swallowed, get medical help or contact a Poison Control Center right away.

Directions

- wet bar with water
- lather vigorously and wash skin
- rinse and dry thoroughly

Inactive ingredients
Soap [Sodium Palmate* · Sodium Cocoate* · Sodium Palm Kernelate*] · Water · Glycerin · Coconut Acid* · Palm Acid* · Palm Kernel Acid* · Stearic Acid* · Fragrance · Sorbitol · Sodium Chloride · Titanium Dioxide · Tetrasodium Glutamate Diacetate · Alcohol · Violet 2 · Red 33
*Contains one or more of these ingredients

Questions? 1-800-258-DIAL (3425)

Visit our website at www.dialsoap.com

Made in Columbia

Henkel®, TM, ©2023 Distributed by

Henkel Corporation, Rocky Hill, CT 06067